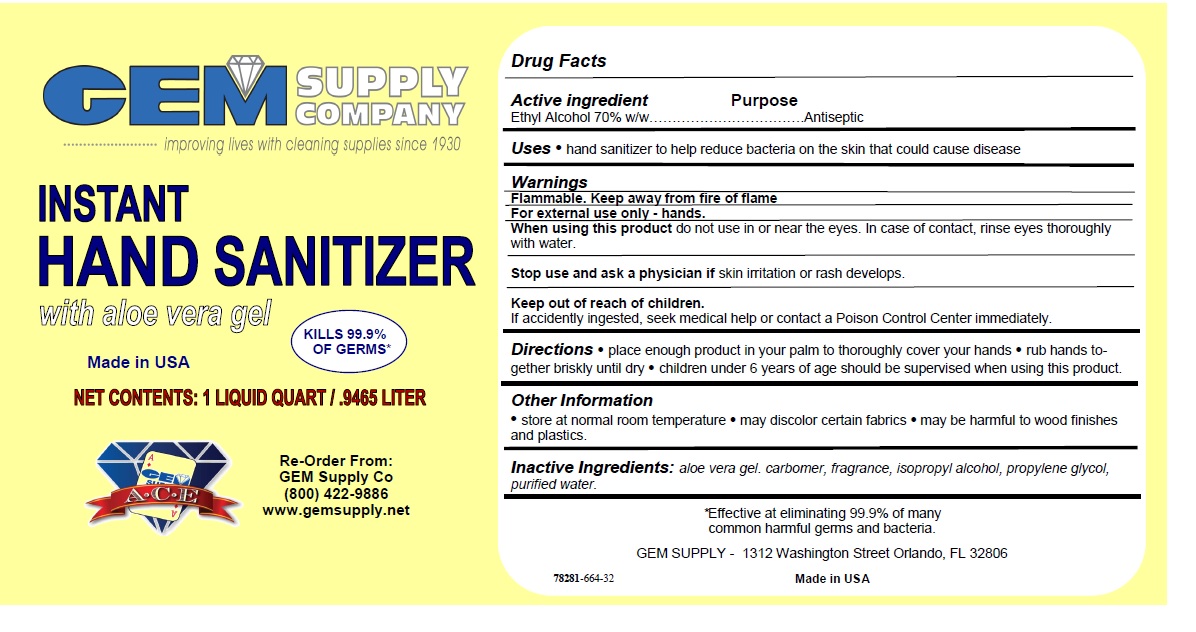 DRUG LABEL: INSTANT HAND SANITIZER
NDC: 78281-664 | Form: GEL
Manufacturer: Gem Supply Company
Category: otc | Type: HUMAN OTC DRUG LABEL
Date: 20200529

ACTIVE INGREDIENTS: ALCOHOL 70 mL/100 mL
INACTIVE INGREDIENTS: ALOE VERA LEAF; CARBOMER HOMOPOLYMER, UNSPECIFIED TYPE; ISOPROPYL ALCOHOL; PROPYLENE GLYCOL; WATER

INSTANT HAND SANITIZER

Active ingredient

Ethyl Alcohol 70% w/w

Purpose

Antiseptic

Uses

• hand sanitizer to help reduce bacteria on the skin that could cause disease

Warnings

Flammable. Keep away from fire of flame

For external use only - hands.

When using this product do not use in or near the eyes. In case of contact, rinse eyes thoroughly with water.

Stop use and ask a physician if skin irritation or rash develops.

Keep out of reach of children.

If accidently ingested, seek medical help or contact a Poison Control Center immediately.

Directions

• place enough product in your palm to thoroughly cover your hands • rub hands together briskly until dry • children under 6 years of age

should be supervised when using this product.

Other Information

• store at normal room temperature • may discolor certain fabrics • may be harmful to wood finishes and plastics.

Inactive Ingredients:

aloe vera gel. carbomer, fragrance, isopropyl alcohol, propylene glycol, purified water.

improving lives with cleaning supplies since 1930

with aloe vera gel

KILLS 99.9% OF GERMS*

Made in USA

Re-Order From:
GEM Supply Co
(800) 422-9886
www.gemsupply.net

*Effective at eliminating 99.9% of many common harmful germs and bacteria.

GEM SUPPLY - 1312 Washington Street Orlando, FL 32806